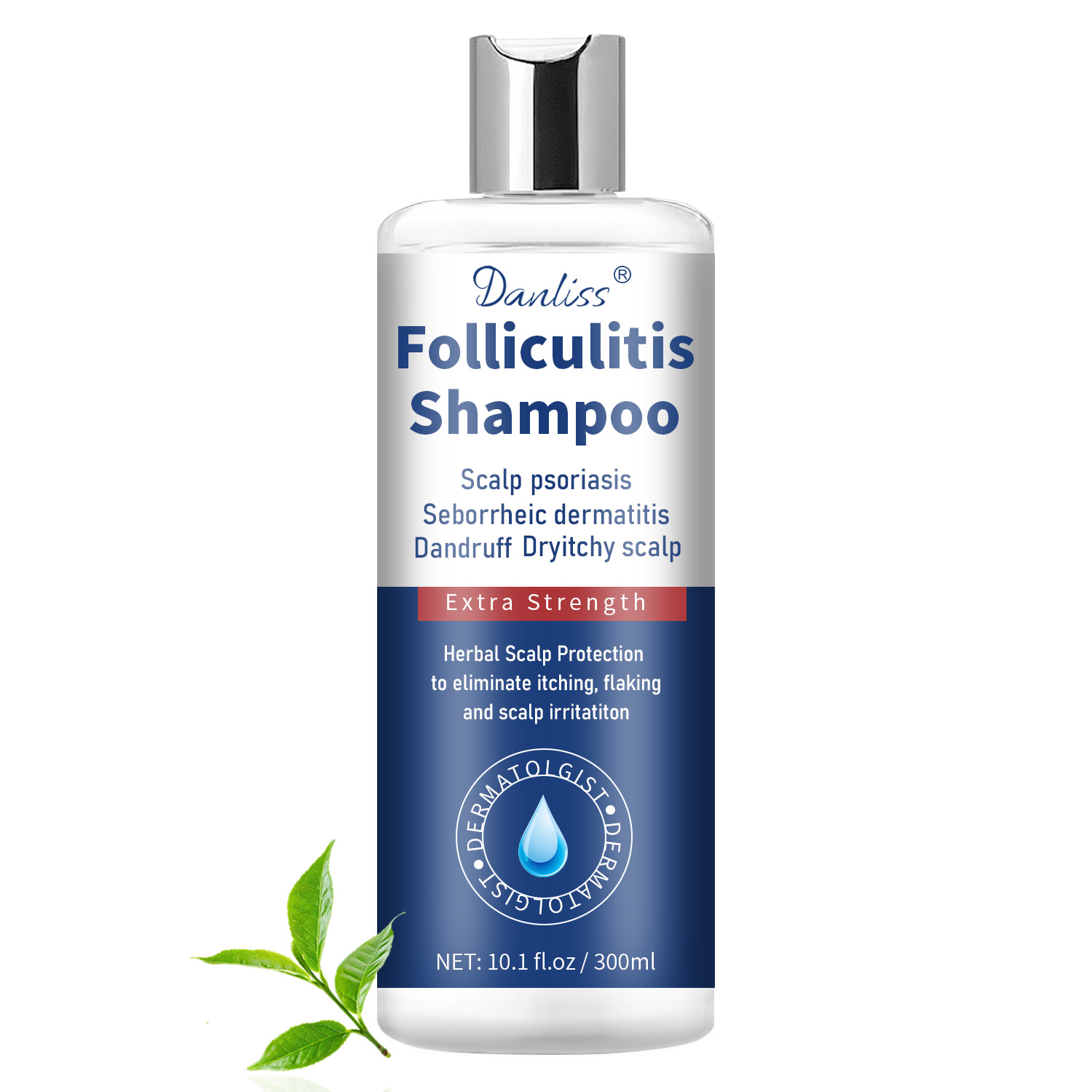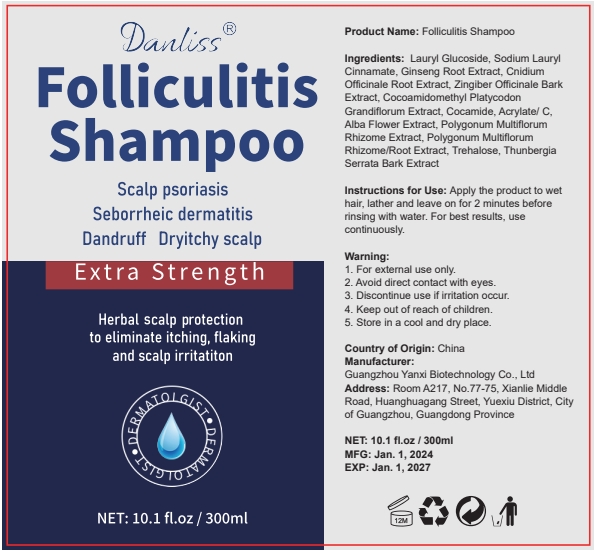 DRUG LABEL: FolliculitisShampoo
NDC: 84025-323 | Form: LIQUID
Manufacturer: Guangzhou Yanxi Biotechnology Co., Ltd
Category: otc | Type: HUMAN OTC DRUG LABEL
Date: 20250311

ACTIVE INGREDIENTS: TREHALOSE 3 mg/300 mL; COCAMIDE 5 mg/300 mL
INACTIVE INGREDIENTS: WATER

DOSAGE AND ADMINISTRATION

Apply the product to wet hair, lather and leave on for 2 minutes before rinsing with water.

WARNINGS

Keep out of children

INACTIVE INGREDIENT

Aqua

INDICATIONS AND USAGE

For daily hair care

Keep out of children

PURPOSE

Cleaning and Nourishing hair